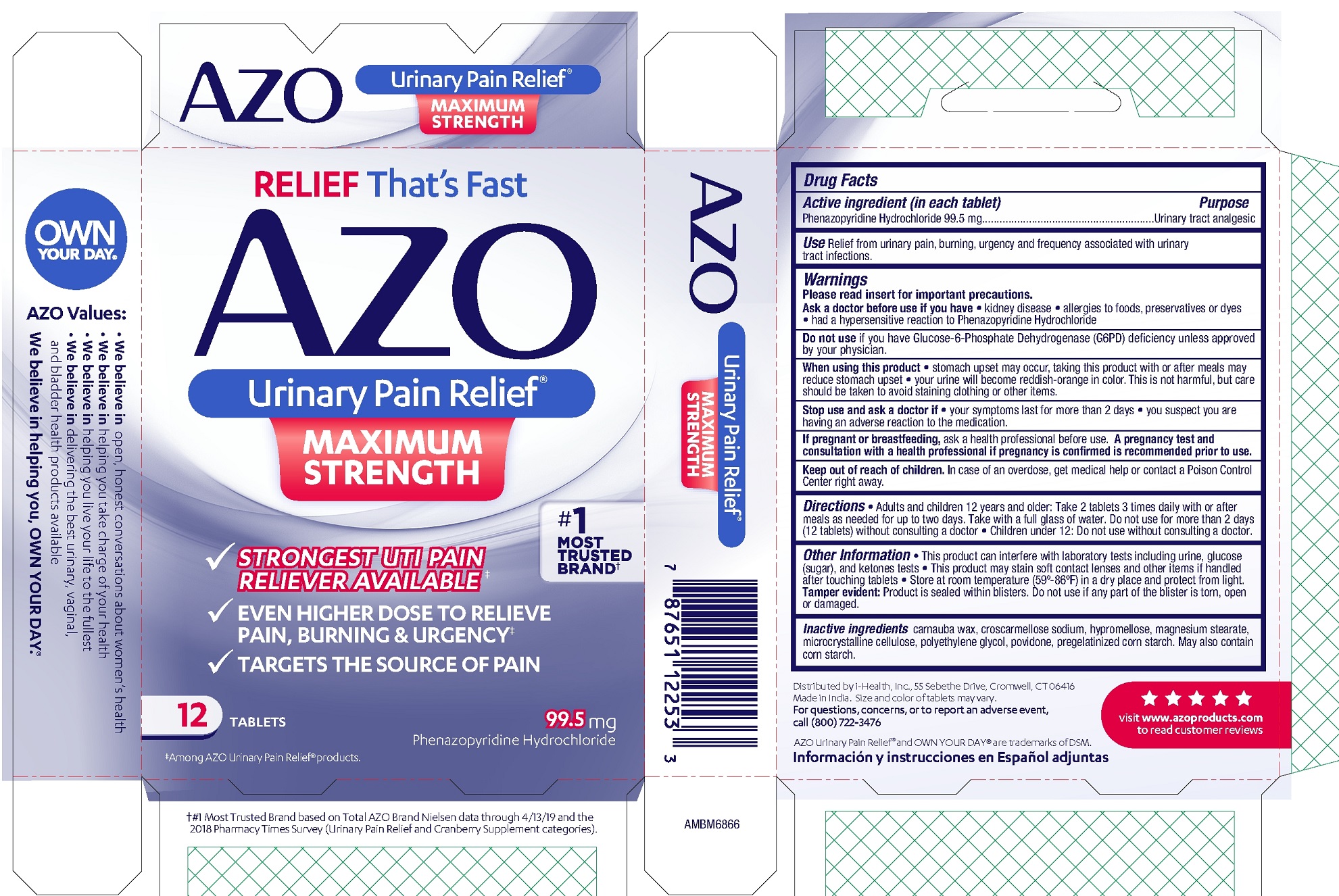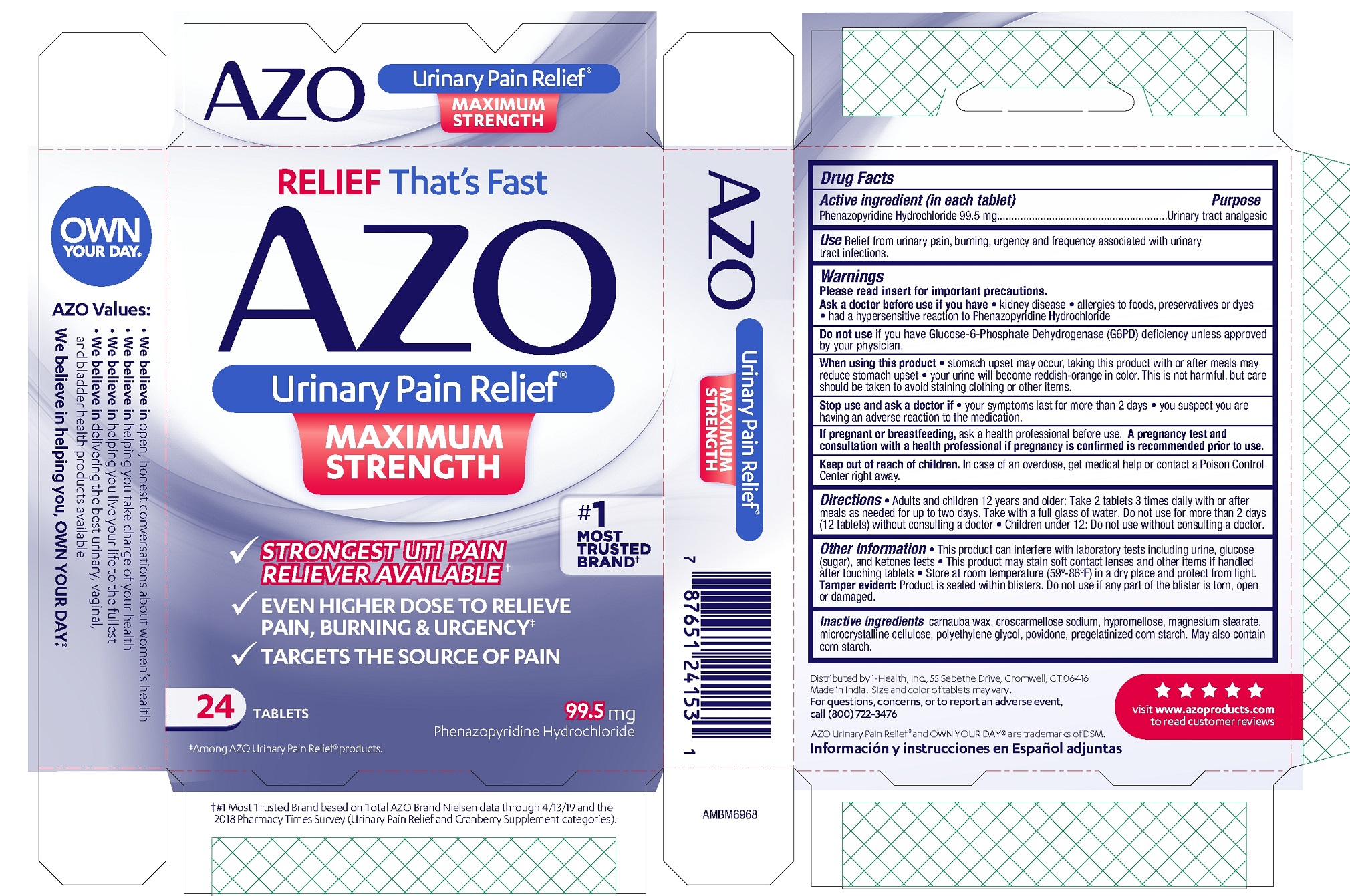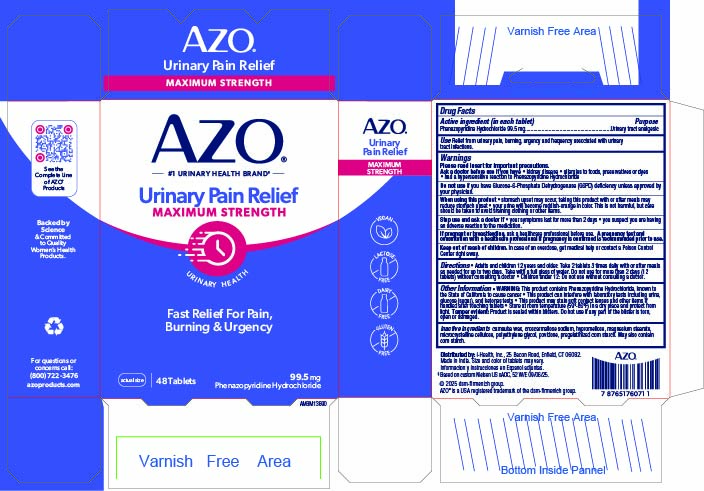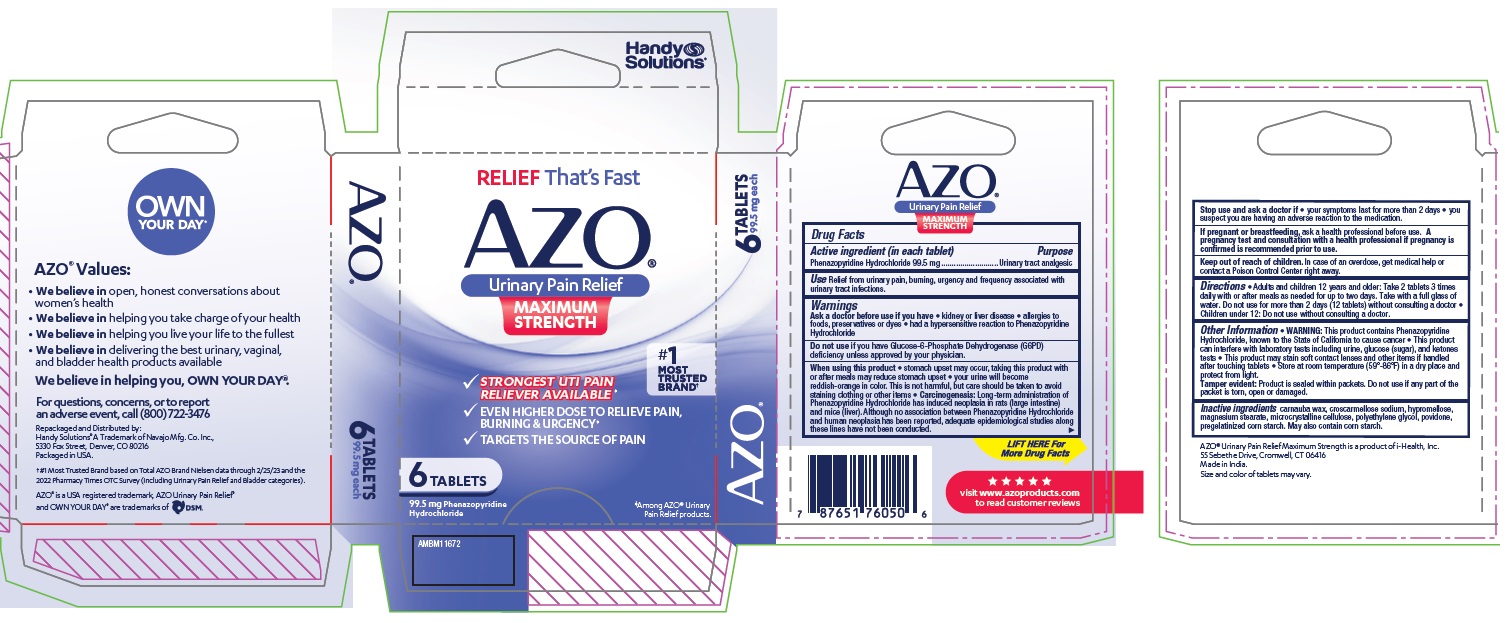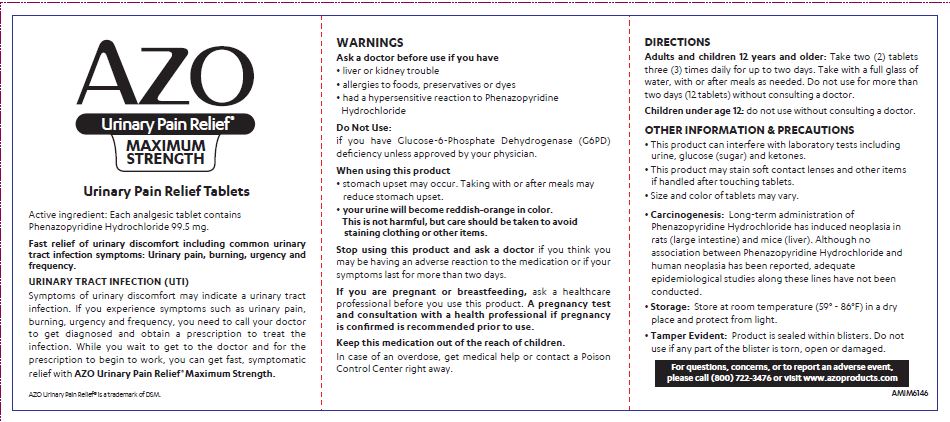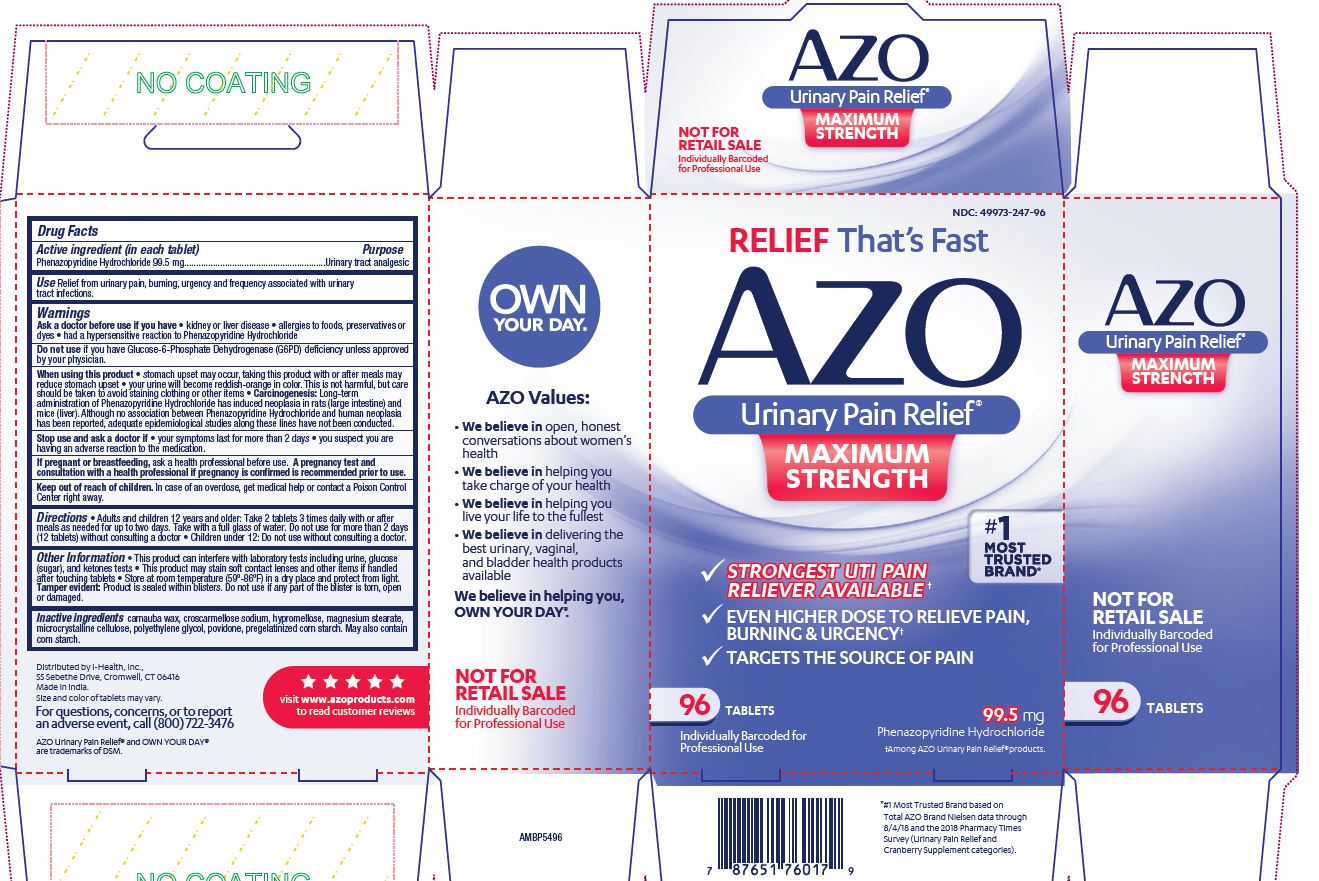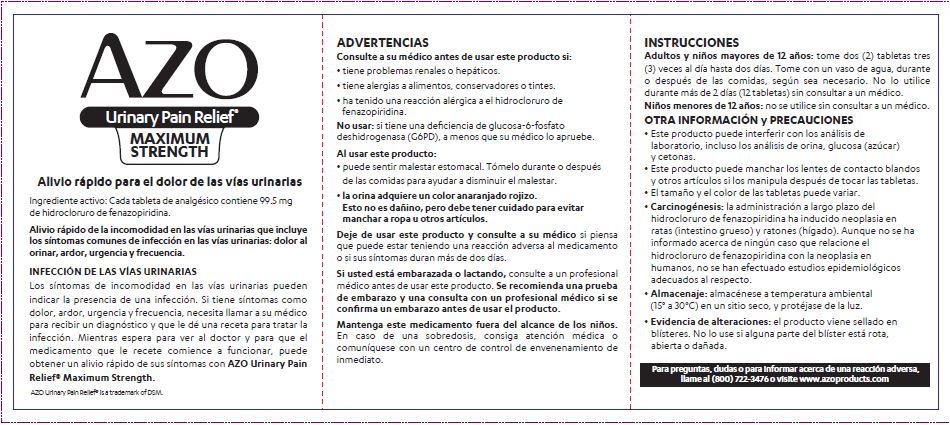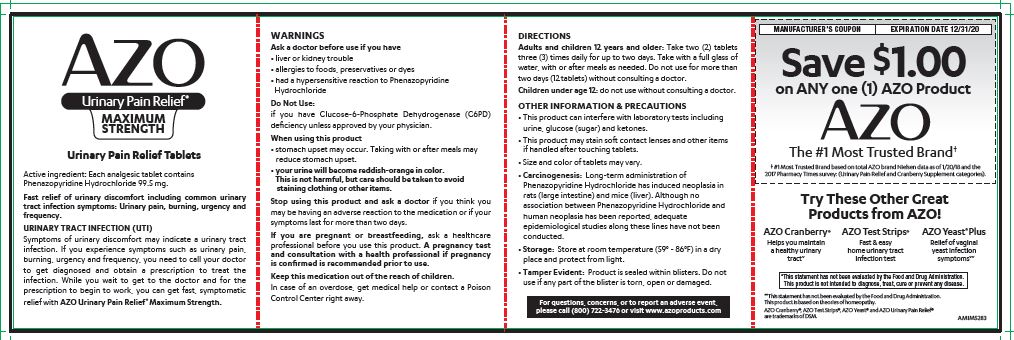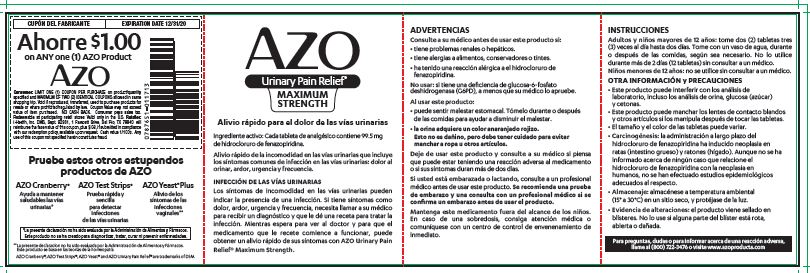 DRUG LABEL: AZO Urinary Pain Relief
NDC: 49973-247 | Form: TABLET
Manufacturer: i-Health, Inc.
Category: otc | Type: HUMAN OTC DRUG LABEL
Date: 20251117

ACTIVE INGREDIENTS: PHENAZOPYRIDINE HYDROCHLORIDE 99.5 mg/1 1
INACTIVE INGREDIENTS: MICROCRYSTALLINE CELLULOSE; STARCH, CORN; HYPROMELLOSE, UNSPECIFIED; POVIDONE, UNSPECIFIED; CROSCARMELLOSE SODIUM; POLYETHYLENE GLYCOL, UNSPECIFIED; CARNAUBA WAX; MAGNESIUM STEARATE

AZO Urinary Pain Relief Maximum Strength

Active ingredient (in each tablet)

Phenazopyridine Hydrochloride 99.5 mg

Purpose

Urinary tract analgesic

INDICATIONS AND USAGE

Use Relief from urinary pain, burning, urgency and frequency associated with urinary tract infections.

Warnings

Please read insert for important precautions.

Ask a doctor before use if you have

- kidney disease
- allergies to foods, preservatives or dyes
- had a hypersensitive reaction to Phenazopyridine Hydrochloride

DO NOT USE

Do not useif you have Glucose-6-Phosphate Dehydrogenase (G6PD) deficiency unless approved by your physician.

When using this product

- stomach upset may occur, taking this product with or after meals may reduce stomach upset
- your urine will become reddish-orange in color. This is not harmful, but care should be taken to avoid staining clothing or other items.

Stop use and ask doctor if

- your symptoms last for more than 2 days
- you suspect you are having an adverse reaction to the medication.

PREGNANCY OR BREAST FEEDING

If pregnant or breastfeeding,ask a professional before use. A pregnancy test and consultation with a health professional if pregnancy is confirmed is recommended prior to use.

Keep out of reach of children. In case of an overdose, get medical help or contact a Poison Control Center right away.

Directions

- Adults and children 12 years and older: Take 2 tablets 3 times daily with or after meals as needed for up to two days. Take with a full glass of water. Do not use for more than 2 days (12 tablets) without consulting a doctor.
- Children under 12: Do not use without consulting a doctor.

Other Inf ormation

- This product can interfere with laboratory tests including urine, glucose (sugar), and ketones tests
- This product may stain soft contact lenses and other items if handled after touching tablets
- Store at room temperature (59-86 F) in a dry place and protect from light.

Tamper evident: Product is sealed within blisters. Do not use if any part of the blister is torn, open or damaged.

INACTIVE INGREDIENT

Inactive ingredients carnauba wax, croscarmellose sodium, hypromellose, magnesium stearate, microcrystalline cellulose, polyethylene glycol, povidone, pregelatinized corn starch. May also contain corn starch.

Distributed by i-Health, Inc., 25 Bacon Road, Enfield, CT 06082

Made in India. Size and color of tablets may vary.

For questions, concerns, or to report an adverse event, call (800) 722-3476

AZO Urinary Pain Relief®and OWN YOUR DAY™ are trademarks of DSM.

Información y instrucciones en Español adjuntas

visit www.azoproducts.comto read customer reviews

PATIENT INFORMATION

AZO

Urinary Pain Relief®

MAXIMUM STRENGTH

Urinary Pain Relief Tablets

Active ingredient: Each analgesic tablet contains Phenazopyridine Hydrochloride 99.5 mg.

Fast relief of urinary discomfort including common urinary tract infection symptoms: Urinary pain, burning, urgency and frequency.

URINARY TRACT INFECTION (UTI)

Symptoms of urinary discomfort may indicate a urinary tract infection. If you experience symptoms such as urinary pain, burning, urgency and frequency, you need to call your doctor to get diagnosed and obtain a prescription to treat the infection. While you wait to get to the doctor and for the prescription to begin to work, you can get fast, symptomatic relief with AZO Urinary Pain Relief Maximum Strength.

WARNINGS

Ask a doctor before use if you have:

- liver or kidney trouble
- allergies to foods, preservatives or dyes
- had a hypersensative reaction to Phenazopyridine Hydrochloride

Do Not Use:

if you have Glucose-6-Phosphate Dehydrogenase (G6PD) deficiency unless approved by your physician.

When using this product

- stomach upset may occur. Taking with or after meals may reduce stomach upset.
- your urine will become reddish-orange in color. This is not harmful, but care should be taken to avoid staining clothing or other items.

Stop using ths product and ask a doctorif you think you may be having an adverse reaction to the medication or if your symptoms last for more than two days.

If you are pregnant or breastfeeding, ask a healthcare professional before you use this product. A pregnancy test and consultation with a health professional if pregnancy is confirmed is recommended prior to use.

Keep this medication out of the reach of children.

In case of an overdose, get medical help or contact a Poison Control Center right away.

DIRECTIONS

Adults and children 12 years and older: Take two (2) tablets three (3) times daily for up to two days. Take with a full glass of water, with or after meals as needed. Do not use for more than two days (12 tablets) without consulting a doctor.

Children under age 12: do not use without consulting a doctor.

OTHER INFORMATION & PRECAUTIONS

- This product can interfere with laboratory tests including urine, glucose (sugar) and keytones.
- This product may stain soft contact lenses and other items if handled after touching tablets.
- Size and color of tablets may vary.
- Carcinogenesis: Long-term administration of Phenazopyridine Hydrochloride has induced neoplasia in rats (large intestine) and mice (liver). Although no association between Phenazopyridine Hydrochloride and human neoplasia has been reported, adequate epidemiological studies along these lines have not been conducted.
- Storage: Store at room temperature (59° - 86°F) in a dry place and protect from light.
- Tamper Evident: Product is sealed within blisters. Do not use if any part of the blister is torn, open or damanged.

For questions, concerns, or to report an adverse event, please call (800) 722-3476 or visit www.azoproducts.com

AZO

Urinary Pain Relief®

MAXIMUM STRENGTH

Alivio rápido para el dolor de las vías urinarias

Ingrediente activo: Cada tableta de analgésico contiene 99.5 mg

de hidrocloruro de fenazopiridina.

Alivio rápido de la incomodidad en las vías urinarias que incluye

los síntomas comunes de infección en las vías urinarias: dolor al

orinar, ardor, urgencia y frecuencia.

INFECCIÓN DE LAS VÍAS URINARIAS

Los síntomas de incomodidad en las vías urinarias pueden

indicar la presencia de una infección. Si tiene síntomas como

dolor, ardor, urgencia y frecuencia, necesita llamar a su médico

para recibir un diagnóstico y que le dé una receta para tratar la

infección. Mientras espera para ver al doctor y para que el

medicamento que le recete comience a funcionar, puede

obtener un alivio rápido de sus síntomas con AZO Urinary Pain

Relief® Maximum Strength.

ADVERTENCIAS

Consulte a su médico antes de usar este producto si:

•tiene problemas renales o hepáticos.

•tiene alergias a alimentos, conservadores o tintes.

•ha tenido una reacción alérgica a el hidrocloruro de

fenazopiridina.

No usar: si tiene una deficiencia de glucosa-6-fosfato

deshidrogenasa (G6PD), a menos que su médico lo apruebe.

Al usar este producto:

•puede sentir malestar estomacal. Tómelo durante o después

de las comidas para ayudar a disminuir el malestar.

• la orina adquiere un color anaranjado rojizo.

Esto no es dañino, pero debe tener cuidado para evitar

manchar a ropa u otros artículos.

Deje de usar este producto y consulte a su médicosi piensa

que puede estar teniendo una reacción adversa al medicamento

o si sus síntomas duran más de dos días.

Si usted está embarazada o lactando, consulte a un profesional

médico antes de usar este producto. Se recomienda una prueba

de embarazo y una consulta con un profesional médico si se

confirma un embarazo antes de usar el producto.

Mantenga este medicamento fuera del alcance de los niños.

En caso de una sobredosis, consiga atención médica o

comuníquese con un centro de control de envenenamiento de

inmediato.

INSTRUCCIONES

Adultos y niños mayores de 12 años: tome dos (2) tabletas tres

(3) veces al día hasta dos días. Tome con un vaso de agua, durante

o después de las comidas, según sea necesario. No lo utilice

durante más de 2 días (12 tabletas) sin consultar a un médico.

Niños menores de 12 años: no se utilice sin consultar a un médico.

OTRA INFORMACIÓN y PRECAUCIONES

•Este producto puede interferir con los análisis de

laboratorio, incluso los análisis de orina, glucosa (azúcar)

y cetonas.

•Este producto puede manchar los lentes de contacto blandos

y otros artículos si los manipula después de tocar las tabletas.

•El tamaño y el color de las tabletas puede variar.

• Carcinogénesis: la administración a largo plazo del

hidrocloruro de fenazopiridina ha inducido neoplasia en

ratas (intestino grueso) y ratones (hígado). Aunque no se ha

informado acerca de ningún caso que relacione el

hidrocloruro de fenazopiridina con la neoplasia en

humanos, no se han efectuado estudios epidemiológicos

adecuados al respecto.

• Almacenaje: almacénese a temperatura ambiental

(15° a 30°C) en un sitio seco, y protéjase de la luz.

•Evidencia de alteraciones: el producto viene sellado en

blísteres. No lo use si alguna parte del blíster está rota,

abierta o dañada.

Para preguntas, dudas o para informar acerca de una reacción adversa,

llame al (800) 722-3476 o visite www.azoproducts.com

Packaging

RELIEF That's Fast

AZO

Urinary Pain Relief®

MAXIMUM STRENGTH

- STRONGEST UTI PAIN RELIEVER AVAILABLE+
- EVEN HIGHER DOSE TO RELEIVE PAIN, BURNING & URGENCY+
- TARGETS THE SOURCE OF PAIN

#1 MOST TRUSTED BRAND*

__ TABLETS

99.5 mg

Phenazopyridine Hydrochloride

+Among AZO Urinary Pain Relief® products.

* #1 Most Trusted Brand based on Total AZO Brand Nielsen data through 10/04/25 and the 2025 Pharmacy Times Survey (Urinary Pain Relief and Cranberry Supplement categories).